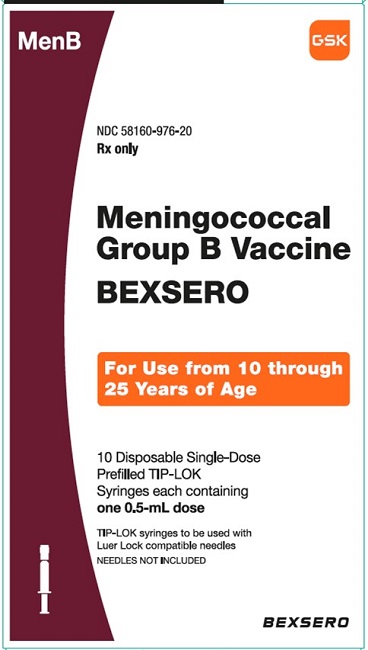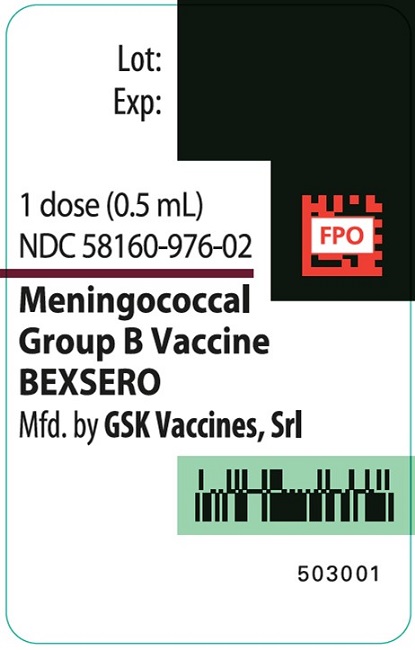 DRUG LABEL: Bexsero
NDC: 58160-976 | Form: INJECTION, SUSPENSION
Manufacturer: GlaxoSmithKline Biologicals SA
Category: other | Type: VACCINE LABEL
Date: 20240819

ACTIVE INGREDIENTS: NEISSERIA MENINGITIDIS GROUP B NHBA FUSION PROTEIN ANTIGEN 50 ug/0.5 mL; NEISSERIA MENINGITIDIS GROUP B FHBP FUSION PROTEIN ANTIGEN 50 ug/0.5 mL; NEISSERIA MENINGITIDIS GROUP B NADA PROTEIN ANTIGEN 50 ug/0.5 mL; NEISSERIA MENINGITIDIS GROUP B STRAIN NZ98/254 OUTER MEMBRANE VESICLE ANTIGEN 25 ug/0.5 mL
INACTIVE INGREDIENTS: ALUMINUM HYDROXIDE; SODIUM CHLORIDE; HISTIDINE; SUCROSE; WATER

HIGHLIGHTS OF PRESCRIBING INFORMATION

These highlights do not include all the information needed to use BEXSERO safely and effectively. See full prescribing information for BEXSERO.
BEXSERO (Meningococcal Group B Vaccine) injectable suspension, for intramuscular use
Initial U.S. Approval: 2015

RECENT MAJOR CHANGES

Indications and Usage (1) | 8/2024
Dosage and Administration, Dose and Schedule (2.1) | 8/2024

1 INDICATIONS AND USAGE

BEXSERO is a vaccine indicated for active immunization to prevent invasive disease caused by Neisseria meningitidis serogroup B. BEXSERO is approved for use in individuals aged 10 through 25 years. (1)

2 DOSAGE AND ADMINISTRATION

For intramuscular use. (2)

Two-dose schedule: Administer a dose (0.5 mL) at 0 and 6 months. If the second dose is administered earlier than 6 months after the first dose, a third dose should be administered at least 4 months after the second dose. (2.1)

Three-dose schedule: Administer a dose (0.5 mL) at 0, 1-2, and 6 months. (2.1)

3 DOSAGE FORMS AND STRENGTHS

Injectable suspension. A single dose is 0.5 mL. (3)

4 CONTRAINDICATIONS

Severe allergic reaction (e.g., anaphylaxis) to any component of BEXSERO or after a previous dose of BEXSERO. (4)

6 ADVERSE REACTIONS

The most commonly reported (≥10%) solicited adverse reactions were pain at the injection site (87%-92%), fatigue (45%-49%), headache (37%-41%), nausea (11%-13%), erythema (10%-15%), myalgia (10%-14%), and swelling (10%-14%). (6.1)

To report SUSPECTED ADVERSE REACTIONS, contact GlaxoSmithKline at 1-888-825-5249 or VAERS at 1-800-822-7967 or www.vaers.hhs.gov.

FULL PRESCRIBING INFORMATION

1 INDICATIONS AND USAGE

BEXSERO is a vaccine indicated for active immunization to prevent invasive disease caused by Neisseria meningitidis serogroup B. BEXSERO is approved for use in individuals aged 10 through 25 years.

2 DOSAGE AND ADMINISTRATION

For intramuscular use.

2.1 Dose and Schedule

Two-dose schedule: Administer a dose (0.5 mL) at 0 and 6 months. If the second dose is administered earlier than 6 months after the first dose, a third dose should be administered at least 4 months after the second dose.

Three-dose schedule: Administer a dose (0.5 mL) at 0, 1-2, and 6 months.

The choice of dosing schedule may depend on the risk of exposure and the individual’s susceptibility to meningococcal serogroup B disease.

2.2 Administration

Shake the syringe immediately before use to form a homogeneous suspension. Do not use the vaccine if it cannot be resuspended. Parenteral drug products should be inspected visually for particulate matter and discoloration prior to administration, whenever solution and container permit. Do not use if particulate matter or discoloration is found.

Administer BEXSERO as a 0.5-mL intramuscular injection.

2.3 Use of BEXSERO with Other Meningococcal Group B Vaccines

Sufficient data are not available on the safety and effectiveness of using BEXSERO and other meningococcal group B vaccines interchangeably to complete the vaccination series.

3 DOSAGE FORMS AND STRENGTHS

BEXSERO is an injectable suspension. A single dose is 0.5 mL.

4 CONTRAINDICATIONS

Do not administer BEXSERO to individuals with a history of a severe allergic reaction (e.g., anaphylaxis) to any component of BEXSERO or after a previous dose of BEXSERO [see Description (11)].

5 WARNINGS AND PRECAUTIONS

5.1 Management of Allergic Reactions

Appropriate medical treatment must be immediately available to manage potential anaphylactic reactions following administration of BEXSERO.

5.2 Syncope

Syncope (fainting) can occur in association with administration of BEXSERO. Ensure procedures are in place to avoid injury from falling associated with syncope.

5.3 Limitation of Vaccine Effectiveness

BEXSERO may not protect all vaccine recipients. BEXSERO may not provide protection against all meningococcal serogroup B strains [see Clinical Pharmacology (12.1)].

5.4 Altered Immunocompetence

Some individuals with altered immunocompetence may have reduced immune responses to BEXSERO.

Complement Deficiency

Persons with certain complement deficiencies and persons receiving treatment that inhibits terminal complement activation (for example, eculizumab) are at increased risk for invasive disease caused by N. meningitidis serogroup B even if they develop antibodies following vaccination with BEXSERO. [See Clinical Pharmacology (12.1).]

6 ADVERSE REACTIONS

The most commonly reported (≥10%) solicited adverse reactions in a Phase 3 clinical trial (Study 1) were pain at the injection site (87%-92%), fatigue (45%-49%), headache (37%-41%), nausea (11%-13%), erythema (10%-15%), myalgia (10%-14%), and swelling (10%-14%).

6.1 Clinical Trials Experience

The safety of BEXSERO was evaluated in 5 clinical studies (Table 1) in which a total of 4,861 participants aged 10 through 25 years received at least 1 dose of BEXSERO. Because clinical trials are conducted under widely varying conditions, adverse reaction rates observed in the clinical trials of a vaccine cannot be directly compared with rates in the clinical trials of another vaccine and may not reflect the rates observed in practice.

Table 1. BEXSERO Clinical Studies
Study; (NCT#) | Participant Age Range | Countries | BEXSERO Recipientsa
Study 1; (NCT04502693) | 10-25 years | United States (U.S.), Australia, Canada, Czech Republic, Estonia, Finland, and Turkey | 1,803
Study 2; (NCT01423084) | 11-17 years | Canada and Australia | 342
Study 3; (NCT01214850) | 18-24 years | United Kingdom (U.K.) | 974
Study 4; (NCT00661713) | 11-17 years | Chile | 1,622
Study 5; (NCT01272180) | 10-25 years | U.S. and Poland | 120
a Recipients who received at least 1 dose of BEXSERO.

In Study 1, conducted in the United States (U.S.), Australia, Canada, Czech Republic, Estonia, Finland, and Turkey, 1,803 participants aged 10 through 25 years received at least 1 dose of BEXSERO either as a 0-, 2-, 6-month schedule (n = 897) or 0-, 6-month schedule (n = 906). A single dose of MENVEO [Meningococcal (Groups A, C, Y, and W-135) Oligosaccharide Diphtheria CRM197 Conjugate Vaccine] was administered 1 month after the third dose in the 0-, 2-, 6-month group and 2 months after the first dose of BEXSERO in the 0-, 6-month group (these participants received saline placebo at month 7). A separate group (n = 178) received a single dose of MENVEO followed 6 months later by 2 doses of BEXSERO administered 1 month apart (these participants received saline placebo at month 2). Approximately 30% of participants were from the U.S. In this trial, the median age was 16 years, males comprised 47%, and 89% of participants were White, 5% were Asian, 4% were Black, and 2% were of other racial groups. Among study participants, 5% were Hispanic.

In Study 2, an uncontrolled study conducted in Canada and Australia, 342 participants aged 11 through 17 years received at least 1 dose of BEXSERO, including 338 participants who received 2 doses of BEXSERO 1 month apart (unapproved dosing schedule). The median age was 13 years, males comprised 55%, and 80% of participants were White, 10% were Asian, 4% were Native American/Alaskan, and 4% were of other racial groups.

In Study 3, conducted in the United Kingdom (U.K.), 974 university students aged 18 through 24 years received at least 1 dose of BEXSERO, including 932 participants who received 2 doses of BEXSERO 1 month apart (unapproved dosing schedule). Comparator groups received 1 dose of MENVEO followed by 1 dose of placebo containing aluminum hydroxide (n = 956) or 2 doses of IXIARO (Japanese Encephalitis Vaccine, Inactivated, Adsorbed) (n = 947). Across groups, median age was 20 years, males comprised 46%, and 88% of participants were White, 5% were Asian, 2% were Black, <1% were Hispanic, and 4% were of other racial groups.

In Study 4, conducted in Chile, 1,622 participants aged 11 through 17 years received at least 1 dose of BEXSERO according to approved and unapproved dosing schedules. A control group of 128 participants received at least 1 dose of placebo containing aluminum hydroxide. In this study, median age was 14 years, males comprised 44%, and 99% were Hispanic.

In Study 5, conducted in the U.S. and Poland, 120 participants aged 10 through 25 years received at least 1 dose of BEXSERO, including 112 participants who received 2 doses of BEXSERO 2 months apart (unapproved dosing schedule); 97 participants received saline placebo followed by MENVEO. Across groups, the median age was 13 years, males comprised 49%, and 60% of participants were White, 34% were Hispanic, 4% were Black, <1% were Asian, and 2% were of other racial groups.

Local and systemic reactogenicity data were solicited from all participants in the trials with the exception of one trial (Study 3) where they were solicited in a subset of participants only. Reports of unsolicited adverse events occurring within the first 7 days after each vaccination were collected in all trials. Reports of unsolicited adverse events occurring within the 30 days after each vaccination were collected in 2 trials (Study 1, Study 5).

Reports of all serious adverse events, medically attended adverse events, and adverse events leading to premature withdrawal were collected throughout the study period of 2 months (Study 2), 8 months (Study 5), or 12 months (Study 1, Study 3, Study 4).

Solicited Adverse Reactions

The rates of local and systemic adverse reactions reported in Study 1 among participants aged 10 through 25 years following each dose of BEXSERO or a single dose of MENVEO are presented in Table 2.

Table 2. Percentage of Participants Aged 10 through 25 Years Reporting Solicited Local and Systemic Adverse Reactions within 7 Days of BEXSERO or MENVEO, by Dose (Solicited Safety Set, Study 1)
 |  | BEXSERO; (0, 6 Months); % |  | BEXSERO; (0, 2, 6 Months); % |  |  | MENVEO; (Single Dose); %
Solicited Reactiona |  | Dose 1 | Dose 2 | Dose 1 | Dose 2 | Dose 3 | Dose 1
Solicited Reactiona |  | n = 894 | n = 759 | n = 885 | n = 823 | n = 765 | n = 178
Local Adverse Reactions
Pain | Any | 92 | 89 | 91 | 87 | 89 | 38
Pain | Severe | 6 | 8 | 6 | 7 | 11 | 0
Erythema | Any | 10 | 12 | 10 | 11 | 15 | 6
Erythema | Severe | 1 | 1 | 1 | 1 | 2 | 1
Swelling | Any | 10 | 11 | 10 | 12 | 14 | 6
Swelling | Severe | 1 | 2 | 1 | 1 | 1 | 1
Induration | Any | 7 | 8 | 7 | 8 | 7 | 4
Induration | Severe | 2 | 1 | 1 | 1 | 1 | 0
Systemic Adverse Reactions
Fatigue | Any | 46 | 45 | 48 | 45 | 49 | 44
Fatigue | Severe | 1 | 3 | 2 | 2 | 3 | 2
Nausea | Any | 12 | 11 | 13 | 13 | 12 | 15
Nausea | Severe | 1 | 0.4 | 1 | 1 | 0.3 | 1
Myalgia | Any | 12 | 14 | 10 | 14 | 14 | 7
Myalgia | Severe | 1 | 0.4 | 0.2 | 1 | 1 | 0
Arthralgia | Any | 8 | 7 | 6 | 9 | 9 | 10
Arthralgia | Severe | 0.3 | 0 | 0.2 | 1 | 0.4 | 0
Headache | Any | 37 | 37 | 41 | 37 | 40 | 39
Headache | Severe | 1 | 1 | 1 | 2 | 2 | 2
Fever | Any | 2 | 3 | 2 | 3 | 3 | 2
Fever | Severe | 0.1 | 0 | 0.1 | 0 | 0.1 | 1
Study 1: NCT04502693.
a Erythema, swelling, and induration: Any (≥25 mm); Severe (>100 mm). Pain, fatigue, nausea, myalgia, arthralgia, headache: Any includes Mild (transient with no limitation in normal daily activity), Moderate (some limitation in normal daily activity), and Severe (unable to perform normal, daily activity). Fever: Any (≥38.0°C/100.4°F); Severe (≥40.0°C/104.0°F).

Solicited adverse reactions were also collected in 4 additional clinical trials (Studies 2-5) in participants aged 10 through 25 years who received BEXSERO. Pain was the most common local adverse reaction reported (83% to 96%), with severe pain reported by 8% to 29% of participants, across trials. Among the systemic reactions collected, myalgia (37% to 75%), headache (21% to 47%), and fatigue/malaise (17% to 58%) were the most commonly reported systemic reactions across trials.

Unsolicited Adverse Events

In Study 1, unsolicited adverse events (non-serious and serious) that occurred within 7 days of any dose of study vaccination were reported by 14% of participants in the group receiving BEXSERO as a 0-, 6-month schedule (n = 900), 13% of participants in the group receiving BEXSERO as a 0-, 2-, 6-month schedule (n = 893), and 20% of participants in the MENVEO group (n = 178).

A non-serious event of arthritis with onset 10 days after receipt of BEXSERO in a 24-year-old male was assessed as vaccine-related by the study investigator. The participant, later found to be HLA-B27 positive, may be at increased risk for arthritis unrelated to vaccination.

In the other controlled trials (Study 3, Study 4, Study 5) (BEXSERO n = 2,221, control n = 2,204), non-serious unsolicited adverse events that occurred within 7 days of any dose were reported by 439 (20%) participants receiving BEXSERO and 197 (9%) control recipients. Unsolicited adverse reactions that were reported among at least 2% of participants and were more frequently reported in participants receiving BEXSERO than in control recipients were injection site pain, headache, injection site induration unresolved within 7 days, and nasopharyngitis.

Serious Adverse Events

In Study 1, serious adverse events that occurred within 30 days of any dose of study vaccination were reported by 1.2% of participants in the group receiving BEXSERO as a 0-, 6-month schedule (n = 900), 1.0% of participants in the group receiving BEXSERO as a 0-, 2-, 6-month schedule (n = 893), and 0% of participants in the MENVEO group (n = 178). None of these events were considered related to BEXSERO.

Overall, in Studies 2-5, among 3,058 participants aged 10 through 25 years who received at least 1 dose of BEXSERO, 66 (2.1%) participants reported serious adverse events at any time during the trial. In the 3 controlled trials (Study 3, Study 4, Study 5) (BEXSERO n = 2,716, control n = 2,078), serious adverse events within 30 days after any dose were reported in 23 (0.8%) participants receiving BEXSERO and 10 (0.5%) control recipients. In Study 4, among participants who received 3 doses of BEXSERO (n = 628), 15 (2.4%) participants reported serious adverse events at any time during the trial.

6.2 Additional Pre-Licensure Safety Experience

In response to outbreaks of serogroup B meningococcal disease at 2 universities in the U.S., BEXSERO was administered as a 2-dose series at least 1 month apart. Information on serious adverse events was collected for a period of 30 days after each dose from 15,351 individuals aged 16 through 65 years who received at least 1 dose. Overall, 50 individuals (0.3%) reported serious adverse events, including one reaction considered related to vaccination, a case of anaphylaxis within 30 minutes following vaccination.

6.3 Postmarketing Experience

The following adverse reactions have been identified during post-approval use of BEXSERO. Because these reactions are reported voluntarily from a population of uncertain size, it is not always possible to reliably estimate their frequency or establish a causal relationship to the vaccine.

Blood and Lymphatic System Disorders

Lymphadenopathy.

General Disorders and Administration Site Conditions

Injection site reactions (including extensive swelling of the vaccinated limb, blisters at or around the injection site, and injection site nodule which may persist for more than 1 month).

Immune System Disorders

Allergic reactions (including anaphylactic reactions), rash, eye swelling.

Nervous System Disorders

Syncope, vasovagal responses to injection.

8 USE IN SPECIFIC POPULATIONS

8.1 Pregnancy

Risk Summary

All pregnancies have a risk of birth defect, loss, or other adverse outcomes. In the U.S. general population, the estimated background risk of major birth defects and miscarriage in clinically recognized pregnancies is 2% to 4% and 15% to 20%, respectively.

There are no adequate and well-controlled studies of BEXSERO in pregnant women in the U.S. Available human data on BEXSERO administered to pregnant women are insufficient to inform vaccine-associated risks in pregnancy.

A developmental toxicity study was performed in female rabbits administered BEXSERO prior to mating and during gestation. The dose was 0.5 mL at each occasion (a single human dose is 0.5 mL). This study revealed no adverse effects on fetal or pre-weaning development due to BEXSERO (see Data).

Data

Animal Data: In a developmental toxicity study, female rabbits were administered BEXSERO by intramuscular injection on Days 29, 15, and 1 prior to mating and on Gestation Days 7 and 20. The total dose was 0.5 mL at each occasion (a single human dose is 0.5 mL). No adverse effects on pre-weaning development up to Postnatal Day 29 were observed. There were no fetal malformations or variations observed.

8.2 Lactation

Risk Summary

It is not known whether the vaccine components of BEXSERO are excreted in human milk. Available data are not sufficient to assess the effects of BEXSERO on the breastfed infant or on milk production/excretion. The developmental and health benefits of breastfeeding should be considered along with the mother’s clinical need for BEXSERO and any potential adverse effects on the breastfed child from BEXSERO or from the underlying maternal condition. For preventive vaccines, the underlying maternal condition is susceptibility to disease prevented by the vaccine.

8.4 Pediatric Use

Safety and effectiveness of BEXSERO have not been established in children younger than 10 years.

8.5 Geriatric Use

Safety and effectiveness of BEXSERO have not been established in adults older than 65 years.

11 DESCRIPTION

BEXSERO (Meningococcal Group B Vaccine) is a sterile, white, opalescent, injectable suspension for intramuscular use. Each 0.5-mL dose of BEXSERO is formulated to contain 50 mcg each of recombinant proteins Neisserial adhesin A (NadA), Neisserial Heparin Binding Antigen (NHBA), and factor H binding protein (fHbp), and 25 mcg of Outer Membrane Vesicles (OMV), 1.5 mg aluminum hydroxide (0.519 mg of Al^3+), 3.125 mg sodium chloride, 0.776 mg histidine, and 10 mg sucrose at pH 6.4 to 6.7.

The NadA component is a fragment of the full-length protein derived from N. meningitidis strain 2996 (peptide 8 variant 2/3)^1. The NHBA component is a recombinant fusion protein comprised of NHBA (peptide 2)^1 and accessory protein 953 derived from N. meningitidis strains NZ98/254 and 2996, respectively. The fHbp component is a recombinant fusion protein comprised of fHbp (variant 1.1)^1 and the accessory protein 936 derived from N. meningitidis strains MC58 and 2996, respectively. These 3 recombinant proteins are individually produced in Escherichia coli and purified through a series of column chromatography steps. The OMV antigenic component is produced by fermentation of N. meningitidis strain NZ98/254 (expressing outer membrane protein Porin A [PorA] serosubtype P1.4)^2, followed by inactivation of the bacteria by deoxycholate, which also mediates vesicle formation. The antigens are adsorbed onto aluminum hydroxide.

Each dose contains less than 0.01 mcg kanamycin (by calculation).

The tip cap and rubber plunger stopper of the prefilled syringe are not made with natural rubber latex.

12 CLINICAL PHARMACOLOGY

12.1 Mechanism of Action

Protection against invasive meningococcal disease is conferred mainly by complement-mediated antibody-dependent killing of N. meningitidis.

NHBA, NadA, and fHbp are proteins found on the surface of meningococci and contribute to the ability of the bacteria to cause disease. OMV derived from the bacterial outer membrane contains PorA and other surface proteins. Vaccination with BEXSERO leads to the production of antibodies directed against NHBA, NadA, fHbp, and OMV. The susceptibility of serogroup B meningococci to complement-mediated antibody-dependent killing following vaccination with BEXSERO is dependent on both the antigenic similarity of the bacterial and vaccine antigens, as well as the amount of antigen expressed on the surface of the invading meningococci.

13 NONCLINICAL TOXICOLOGY

13.1 Carcinogenesis, Mutagenesis, Impairment of Fertility

BEXSERO has not been evaluated for carcinogenic or mutagenic potential or impairment of male fertility in animals.

14 CLINICAL STUDIES

The effectiveness of BEXSERO was assessed by measuring serum bactericidal activity (SBA) in an assay that used endogenous complement preserved in the serum samples collected from study participants (enc-hSBA) and an assay that used an exogenous source of human complement (hSBA).

The enc-hSBA assay was used to assess effectiveness against diverse N. meningitidis serogroup B strains. Participants’ sera were tested for the presence or absence of bactericidal activity to measure breadth of immune response against a panel of 110 diverse U.S. disease-causing N. meningitidis serogroup B strains that were collected between 2000 and 2008. The panel includes most antigen types found among serogroup B isolates circulating in the U.S. between 2000 and 2017, and includes some strains with genetic profiles characterized as hypervirulent. Each participant’s serum was tested at a four-fold dilution against a maximum of 35 strains randomly selected from the panel.

The hSBA assay measured bactericidal activity in participants’ sera against 4 serogroup B indicator strains, one for each of the 4 antigenic components of BEXSERO.

Breadth of Immune Response Elicited by BEXSERO (enc-hSBA Assay)

Study 1 evaluated enc-hSBA responses in participants aged 10 through 25 years 1 month following dose 2 of a 0-, 6-month schedule and dose 3 of a 0-, 2-, 6-month schedule of BEXSERO using responder-based and test-based analyses.

Responder-based analyses (Table 3) evaluated the percentages of participants whose sera killed ≥70% of the tested strains.

Table 3. Percentage of Participants Whose Sera Killed ≥70% of Meningococcal Serogroup B Strains Testeda (Responder-Based) following BEXSERO, Study 1b
Groupc | Dose | N | % Respondersd; (97.5% CI)
0, 6 Months | Dose 2 | 813 | 90; (87e, 92)
0, 2, 6 Months | Dose 3 | 790 | 93; (91e, 95)
Study 1: NCT04502693.
CI = Confidence interval.
a Each participant’s serum was tested for bactericidal activity (yes/no) against a maximum of 35 strains randomly selected from the 110-strain panel.
b Full Analysis Set includes all participants who received at least 1 dose of the study treatment and have post-vaccination immunogenicity data.
c enc-hSBA responses were measured one month after the second dose of BEXSERO using the 0-, 6-month schedule and one month after the third dose of BEXSERO using the 0-, 2-, 6-month schedule.
d % Responders is defined as percentages of participants whose serum kills ≥70% of strains tested using enc-hSBA.
e Predefined criterion (lower limit of the 2-sided 97.5% CI >65%) met. CI calculated using Clopper-Pearson method.

Of the approximately 35 serogroup B strains tested per participant in the enc-hSBA assay at 1 month following vaccination, the median percentage killed by each participant’s serum was 88.2% (25th percentile, 80.0%; 75th percentile, 94.3%) after dose 2 of the 0-, 6-month BEXSERO schedule; 88.6% (25th percentile, 80.0%; 75th percentile, 94.3%) after dose 3 of the 0-, 2-, 6-month BEXSERO schedule; and 17.1% (25th percentile, 11.1%; 75th percentile, 26.7%) after MENVEO.

Test-based analyses (Table 4) evaluated the reduction in relative risk of enc-hSBA tests without bactericidal activity against meningococcal serogroup B strains following BEXSERO as compared to MENVEO.

Table 4. Reduction in Relative Risk of a Testa without Bactericidal Activity against Meningococcal Serogroup B Strains following BEXSERO (Test-Based), Study 1b
Groupc | Dose | Number of Participants | % of Tests without Bactericidal Activity (n/N) | Reduction in Relative Risk of a Test without Bactericidal Activityd,e; %; (97.5% CIe)
BEXSERO; 0, 6 Months | Dose 2 | 764 | 14; (3,777 / 26,142) | 82; (80f, 83)
BEXSERO; 0, 2, 6 Months | Dose 3 | 747 | 13; (3,412 / 25,596) | 83; (82f, 84)
MENVEO | Dose 1 | 133 | 79; (3,456 / 4,374) | -
Study 1: NCT04502693.
CI = Confidence interval, n = number of tests without bactericidal activity, N = total number of tests, RR = Relative Risk.
a Each test qualitatively assessed (yes/no) the bactericidal activity of one participant’s serum against one of the 110 U.S. meningococcal serogroup B strains. Each participant’s serum was tested against a maximum of 35 strains randomly selected from the 110-strain panel.
b Per Protocol Set includes all participants in the Full Analysis Set minus participants with protocol deviations that lead to exclusion from the Per Protocol Set.
c enc-hSBA responses were measured one month after the second dose of BEXSERO using the 0-, 6-month schedule, one month after the third dose of BEXSERO using the 0-, 2-, 6-month schedule, and one month after the single dose of MENVEO.
d Reduction in Relative Risk of enc-hSBA tests without bactericidal activity is defined as 1- RR = (1- percentage of samples without bactericidal serum activity measured by enc-hSBA in the BEXSERO group / percentage of samples without bactericidal serum activity in the MENVEO group) x 100%.
e The Relative Risk and corresponding confidence intervals are estimated using a generalized linear model where treatment group and randomization factors were modeled as independent variables.
f Predefined criterion (lower limit of the 2-sided 97.5% CI >65%) met.

For each individual strain in the 110-strain panel, the percentage of tests with bactericidal activity following BEXSERO ranged from 4% to 100%; the median was 97% (25th percentile, 80%; 75th percentile, 99%) for the 0-, 6-month schedule and 98% (25th percentile, 85%; 75th percentile, 99%) for the 0-, 2-, 6-month schedule. For each individual strain, the percentage of tests with bactericidal activity following MENVEO ranged from 0% to 100%; the median was 12% (25th percentile, 3%; 75th percentile, 28%).

Immune Response to BEXSERO (hSBA Assay)

In Study 1, immune responses in participants aged 10 through 25 years were measured following 0-, 6-month or 0-, 2-, 6-month schedules of BEXSERO with hSBA assays using indicator strains representative of each of the 4 antigenic components of BEXSERO (fHbp, NadA, NHBA, and OMV). The proportion of participants who achieved a 4-fold or greater increase in hSBA titer for each of the 4 strains (seroresponse), and the proportion of participants with a titer greater than or equal to the lower limit of quantitation (LLOQ) of the assay for all 4 strains (composite response) at 1 month after dose 2 (0-, 6-month schedule) and doses 2 and 3 (0-, 2-, 6-month schedule) are shown in Table 5.

Table 5. Percentage of Participants with hSBA Seroresponse and Composite Response following BEXSERO, Study 1a
 | 0, 6 Months |  |  | 0, 2, 6 Months
 | Dose 2 |  |  | Dose 2 |  |  | Dose 3
Seroresponseb,c,d Antigen | N | % | 95% CIe | N | % | 95% CIe | N | % | 95% CIe
fHbp | 699 | 78 | 74, 81 | 739 | 67 | 64, 71 | 679 | 81 | 78, 84
NadA | 700 | 95 | 93, 97 | 738 | 97 | 95, 98 | 679 | 99 | 98, 99
NHBA | 704 | 69 | 66, 72 | 739 | 58 | 55, 62 | 685 | 67 | 63, 70
OMV | 664 | 57 | 53, 61 | 724 | 54 | 50, 57 | 637 | 57 | 53, 60
Composite Responsed,f; Time Point | N | % | 95% CIe | N | % | 95% CIe | N | % | 95% CIe
Baseline; (pre-vaccination) | 708 | 0.6 | 0.2, 1.4 | 727 | 1.1 | 0.5, 2.2 | 727 | 1.1 | 0.5, 2.2
1 Month post-dose 2 or 3 | 683 | 80 | 77, 83 | 744 | 74 | 71, 77 | 654 | 82 | 78, 84
Study 1: NCT04502693.
hSBA = Serum bactericidal activity measured using human complement, CI = Confidence interval, fHbp = factor H binding protein, NadA = Neisserial adhesin A, NHBA = Neisserial Heparin Binding Antigen, OMV = Outer Membrane Vesicles, LOD = Limit of detection, LLOQ = Lower limit of quantitation.
a Full Analysis Set includes all participants who received at least 1 dose of the study treatment and have post-vaccination immunogenicity data.
b Seroresponse is defined as: a post-vaccination hSBA titer at least 4-fold the LOD or ≥LLOQ, whichever is greater, for participants with pre-vaccination hSBA titer <LOD, a post-vaccination hSBA titer at least 4-fold the LLOQ for participants with pre-vaccination hSBA titer ≥LOD and <LLOQ, and a post-vaccination hSBA at least 4-fold the pre-vaccination hSBA titer for participants with pre-vaccination hSBA titer ≥LLOQ.
c Antigen (indicator strain) = fHbp (M14459), NadA (96217), NHBA (M13520), OMV (NZ98/254).
d LOD = 4 for fHbp (M14459); 6 for NadA (96217); 4 for NHBA (M13520); 4 for OMV (NZ98/254). LLOQ = 5 for fHbp (M14459); 14 for NadA (96217); 6 for NHBA (M13520); 6 for OMV (NZ98/254).
e CI calculated using Clopper-Pearson method.
f Composite hSBA Response means hSBA ≥LLOQ for all 4 Meningococcal B indicator strains.

In Study 2 and Study 3, hSBA immune responses were measured with hSBA assays using indicator strains for 3 of the 4 antigenic components of BEXSERO: fHbp (strain H44/76), NadA (strain 5/99), and OMV (strain NZ98/254). A 4-fold hSBA response (seroresponse) was defined as a post-vaccination hSBA titer ≥16 for participants with pre-vaccination hSBA titer <4, a post-vaccination titer at least 4-fold the LLOQ for participants with pre-vaccination hSBA titer ≥4 but <LLOQ, and a post-vaccination hSBA titer 4-fold the pre-vaccination titer for participants with pre-vaccination hSBA titer ≥LLOQ. A composite hSBA response was defined as hSBA ≥LLOQ for all 3 indicator strains (≥1:16 for H44/76 and 5/99; 1:8 for NZ98/254).

In Study 2, Canadian and Australian adolescents aged 11 through 17 years received 2 doses of BEXSERO, administered 1 month apart. Among participants in the evaluable immunogenicity population (N = 298-299), the percentage of participants (95% CI) who demonstrated a 4-fold hSBA response were as follows: fHbp 98% (95%, 99%), NadA 99% (98%, 100%), and OMV 39% (33%, 44%). The percentage of participants with a composite response was 0% at baseline and 63% (95% CI: 57%, 68%) at 1 month following dose 2.

In Study 3, University students in the U.K. aged 18 through 24 years received 2 doses of BEXSERO, administered 1 month apart. Among participants in the evaluable immunogenicity population (N = 147-148), the percentage of participants (95% CI) who demonstrated a 4-fold hSBA response were as follows: fHbp 78% (71%, 85%), NadA 94% (89%, 97%), and OMV 67% (58%, 74%). The percentage of participants with a composite response was 24% (95% CI: 18%, 30%; n = 186) at baseline, 88% (95% CI: 82%, 93%; n = 147) at 1 month following dose 2, and 66% (95% CI: 58%, 72%; n = 136) at 11 months following dose 2.

15 REFERENCES

1. Wang X, et al. Vaccine. 2011; 29:4739-4744.
2. Hosking J, et al. Clin Vaccine Immunol. 2007;14:1393-1399.

16 HOW SUPPLIED/STORAGE AND HANDLING

16.1 How Supplied

BEXSERO is available in 0.5-mL single-dose, disposable, prefilled TIP-LOK syringes (Luer Lock syringes) packaged without needles. TIP-LOK syringes are to be used with Luer Lock compatible needles.

The tip cap and rubber plunger stopper of the prefilled syringe are not made with natural rubber latex.

Table 6. Product Presentation for BEXSERO
Presentation | Carton NDC Number | Components
Prefilled syringe
Carton of 10 syringes | 58160-976-20 | 0.5-mL single-dose prefilled syringe NDC 58160-976-02

16.2 Storage and Handling

Do not freeze. Discard if the vaccine has been frozen.

Store refrigerated, at 36°F to 46°F (2°C to 8°C).

Protect from light.

Do not use after the expiration date.

17 PATIENT COUNSELING INFORMATION

Give the patient, parent, or guardian the Vaccine Information Statements, which are required by the National Childhood Vaccine Injury Act of 1986 to be given prior to immunization. These materials are available free of charge at the Centers for Disease Control and Prevention (CDC) website (www.cdc.gov/vaccines).

Inform patients, parents, or guardians about:

- The importance of completing the immunization series.
- Reporting any adverse reactions to their healthcare provider.

BEXSERO, MENVEO, and TIP-LOK are trademarks owned by or licensed to the GSK group of companies.

The other brand listed is a trademark owned by or licensed to its owner and is not owned by or licensed to the GSK group of companies. The maker of this brand is not affiliated with and does not endorse the GSK group of companies or its products.

Manufactured by GSK Vaccines, Srl

Bellaria-Rosia 53018, Sovicille (SI), Italy

U.S. License No. 1617

Distributed by GlaxoSmithKline

Durham, NC 27701

©2024 GSK group of companies or its licensor.

BXS:8PI

PACKAGE LABEL

PRINCIPAL DISPLAY PANEL

NDC 58160-976-20

BEXSERO

Meningococcal Group B Vaccine

MenB

GSK

Rx Only

For Use from 10 through 25 Years of Age

10 Disposable Single-Dose Prefilled TIP-LOK Syringes each containing one 0.5-mL dose

TIP-LOK syringes to be used with Luer Lock compatible needles

NEEDLES NOT INCLUDED

BEXSERO

Made in Italy

©2023 GSK group of companies or its licensor.

Rev. 08/23
515763

Syringe Label

NDC 58160-976-02

503001